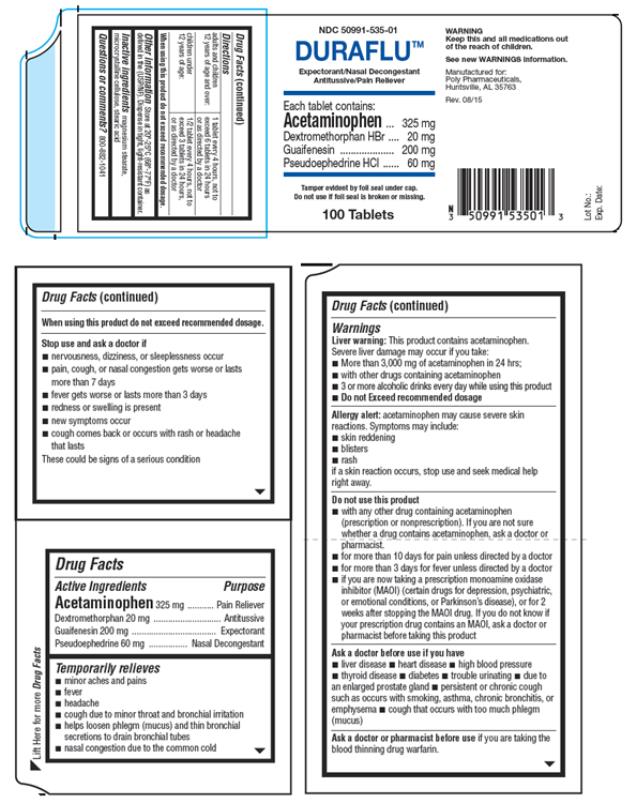 DRUG LABEL: Duraflu
NDC: 50991-535 | Form: TABLET
Manufacturer: Poly Pharmaceuticals, Inc.
Category: otc | Type: HUMAN OTC DRUG LABEL
Date: 20241109

ACTIVE INGREDIENTS: PSEUDOEPHEDRINE HYDROCHLORIDE 60 mg/1 1; ACETAMINOPHEN 325 mg/1 1; DEXTROMETHORPHAN HYDROBROMIDE 20 mg/1 1; GUAIFENESIN 200 mg/1 1
INACTIVE INGREDIENTS: MAGNESIUM STEARATE; CELLULOSE, MICROCRYSTALLINE; STEARIC ACID

Duraflu Tablets

DurafluTablets

Rev. 08/15

Drug Facts

Active Ingredients

Acetaminophen 325 mg
Dextromethorphan HBr 20 mg
Guaifenesin 200 mg
Pseudoephedrine HCl 60 mg

Purpose

Pain Reliever
Antitussive
Expectorant
Nasal Decongestant

Temporarily relieves

- minor aches and pains
- fever
- headache
- cough due to minor throat and bronchial irritation
- helps loosen phlegm (mucus) and thin bronchial secretions to drain bronchial tubes
- nasal congestion due to the common cold

Warnings

Liver warning: This product contains acetaminophen.

Severe liver damage may occur if you take:

- More than 3,000 mg of acetaminophen in 24 hrs;
- with other drugs containing acetaminophen
- 3 or more alcoholic drinks every day while using this product
- Do not Exceed recommended dosage

■ KEEP THIS AND ALL MEDICATION OUT OF REACH OF CHILDREN

Allergy alert: acetaminophen may cause severe skin reactions. Symptoms may include:

- skin reddening
- blisters
- rash

If a skin reaction occurs, stop use and seek medical help right away.

Do not use this product

- with any other drug containing acetaminophen (prescription or nonprescription). If you are not sure whether a drug contains acetaminophen, ask a doctor or pharmacist.
- for more than 10 days for pain unless directed by a doctor
- for more than 3 days for fever unless directed by a doctor
- if you are now taking a prescription monoamine oxidase inhibitor (MAOI) (certain drugs for depression, psychiatric, or emotional conditions, or Parkinson’s disease), or for 2 weeks after stopping the MAOI drug. If you do not know if your prescription drug contains an MAOI, ask a doctor or pharmacist before taking this product

Ask a doctor before use if you have

■ liver disease ■ heart disease ■ high blood pressure ■ thyroid disease ■ diabetes ■ trouble urinating ■ due to an enlarged prostate gland ■ persistent or chronic cough such as occurs with smoking, asthma, chronic bronchitis, or emphysema ■ cough that occurs with too much phlegm (mucus)

Ask a doctor or pharmacist before use

if you are taking the blood thinning drug warfarin.

When using this product

do not exceed recommended dosage.

Stop use and ask a doctor if

- nervousness, dizziness, or sleeplessness occur
- pain, cough, or nasal congestion gets worse or lasts more than 7 days
- fever gets worse or lasts more than 3 days
- redness or swelling is present
- new symptoms occur
- cough comes back or occurs with rash or headache that lasts

These could be signs of a serious condition

Directions

Adults and children 12 years of age and over: | 1 tablet every 4 hours, not to exceed 6 tablets in 24 hours or as directed by a doctor
Children under 12 years of age | ½ tablet every 4 hours, not to exceed 3 tablets in 24 hours, or as directed by a doctor

When using this product do not exceed recommended dosage.

Other information

Store at 20°- 25° Celsius (68° – 77° Fahrenheit) as defined in the (USP/NF). Dispense in tight, light-resistant container.

Inactive ingredients

magnesium stearate, microcrystalline cellulose, stearic acid

Questions or comments?

800-882-1041

Manufactured For:
Poly Pharmaceuticals, Inc.
Huntsville, AL 35763

Rev. 08/15

PRINCIPAL DISPLAY PANEL

NDC 50991-535-01
DURAFLU™
Expectorant/ Nasal Decongestant
Antitussive/Pain Reliever
100 Tablets